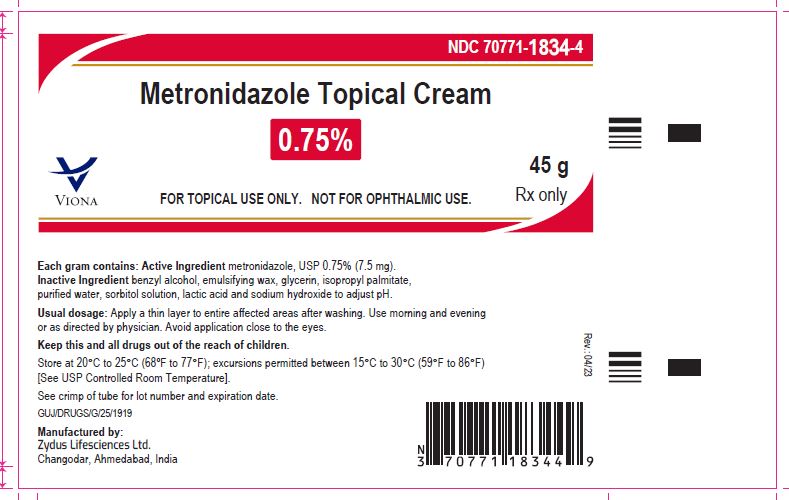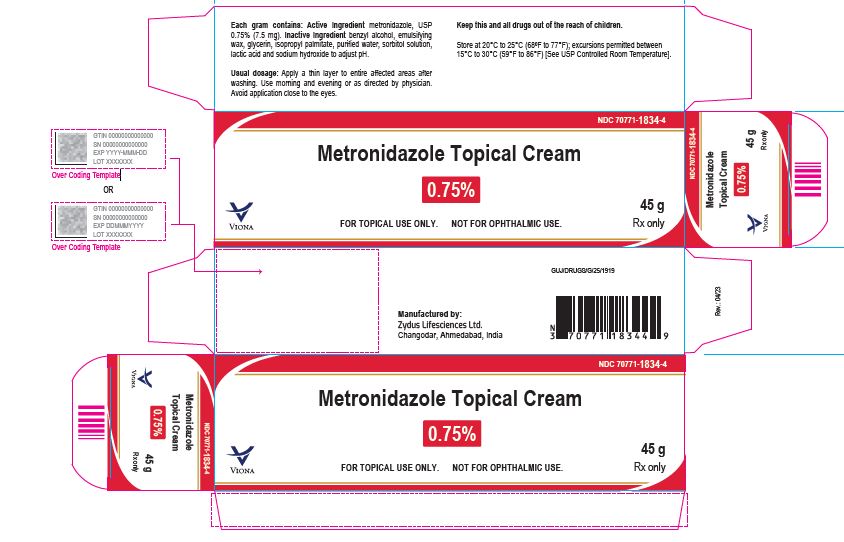 DRUG LABEL: Metronidazole
NDC: 70771-1834 | Form: CREAM
Manufacturer: Zydus Lifesciences Limited
Category: prescription | Type: HUMAN PRESCRIPTION DRUG LABEL
Date: 20230505

ACTIVE INGREDIENTS: METRONIDAZOLE 7.5 mg/1 g
INACTIVE INGREDIENTS: BENZYL ALCOHOL; GLYCERIN; ISOPROPYL PALMITATE; LACTIC ACID; SODIUM HYDROXIDE; SORBITOL SOLUTION; WATER

Metronidazole Topical Cream, 0.75%

PACKAGE LABEL.PRINCIPAL DISPLAY PANEL

NDC 70771-1834-4

Metronidazole Topical Cream, 0.75%

Rx only

45 g